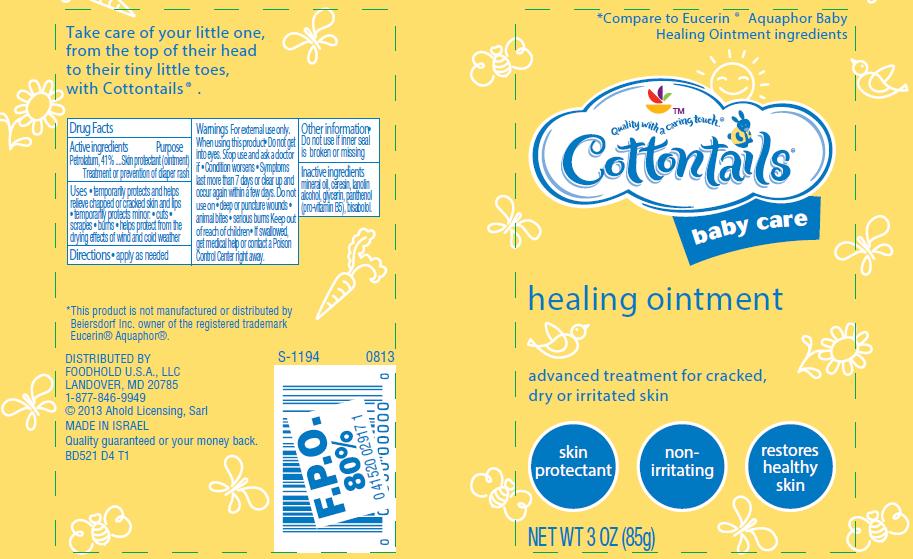 DRUG LABEL: Baby Healing
NDC: 41520-522 | Form: OINTMENT
Manufacturer: American Sales Company
Category: otc | Type: HUMAN OTC DRUG LABEL
Date: 20130924

ACTIVE INGREDIENTS: PETROLATUM 41 g/100 g
INACTIVE INGREDIENTS: MINERAL OIL; CERESIN; LANOLIN; GLYCERIN; PANTHENOL; LEVOMENOL; ALCOHOL

Cottontails baby care healing ointment

Active ingredient

Petrolatum 41%

Purpose

Skin protectant (ointment)

Uses

- treatment or prevention of diaper rash
- temporarily protects and helps relieve chapped or cracked skin and lips
- temporarily protects minor: cuts, scrapes burns
- helps protect from the drying effects of wind and cold weather

Warnings

For external use only. When using this product

- Do not get into eyes. Stop use and ask a doctor if
  Condition worsens
  Symptoms last more than 7 days or clear up and occur again within a few days.
- Do not use on
  deep or puncture wounds
  animal bites
  serious burns
- Keep out of reach of children
- If swallowed, get medical help or contact a Poison Control Center right away.

Directions

Apply as needed

Other information

Do not use if inner seal is broken or missing

Inactive ingredients

mineral oil, ceresin, lanolin, alcohol, glycerin, panthenol (pro-viatmin B5), bisabolol.

Package/Label Principal Display Panel

Cottontails baby care healing ointment

advanced treatment for cracked, dry or irritated skin

*Compare to Eucerin® Aquaphor® Baby Healing Ointment Ingredients

NET WT 3 OZ (85 g)

- Skin Protectant
- Non-Irritating
- Restores healthy skin

*This product is not manufactured or distributed by Beiersdorf Inc. owner of the registered trademark Eucerin® Aquaphor®.

DISTRIBUTED BY FOODHOLD, U.S.A., LLC
LANDOVER, MD 20785 1-877-846-9949
© 2013 Ahold Licensing, Sarl

MADE IN ISRAEL

Quality guaranteed or your money back.

BD521 D4 T1

Tube Label